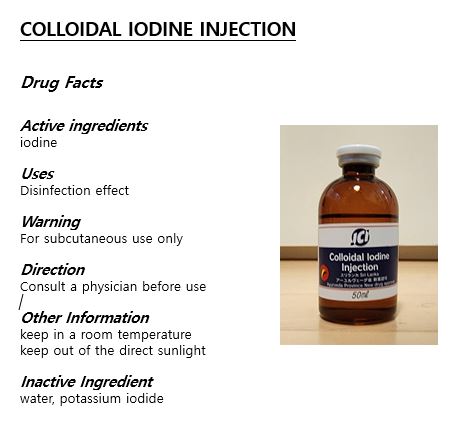 DRUG LABEL: COLLOIDAL IODINEINJECTION
NDC: 69164-0001 | Form: SOLUTION
Manufacturer: JCI Colloidal Iodine Laboratory Co., Ltd.
Category: otc | Type: HUMAN OTC DRUG LABEL
Date: 20230517

ACTIVE INGREDIENTS: IODINE 2 g/100 mL
INACTIVE INGREDIENTS: POTASSIUM IODIDE; WATER

Drug Facts

ACTIVE INGREDIENT

iodine

INACTIVE INGREDIENT

potassium iodide, hydrogen water

PURPOSE

disinfection effect

keep out of reach of the children

INDICATIONS AND USAGE

Consult a physician before use

WARNINGS

For subcutaneous use only

keep in a room temperature

keep out of the direct sunlight

DOSAGE AND ADMINISTRATION

for subcutaneous use only